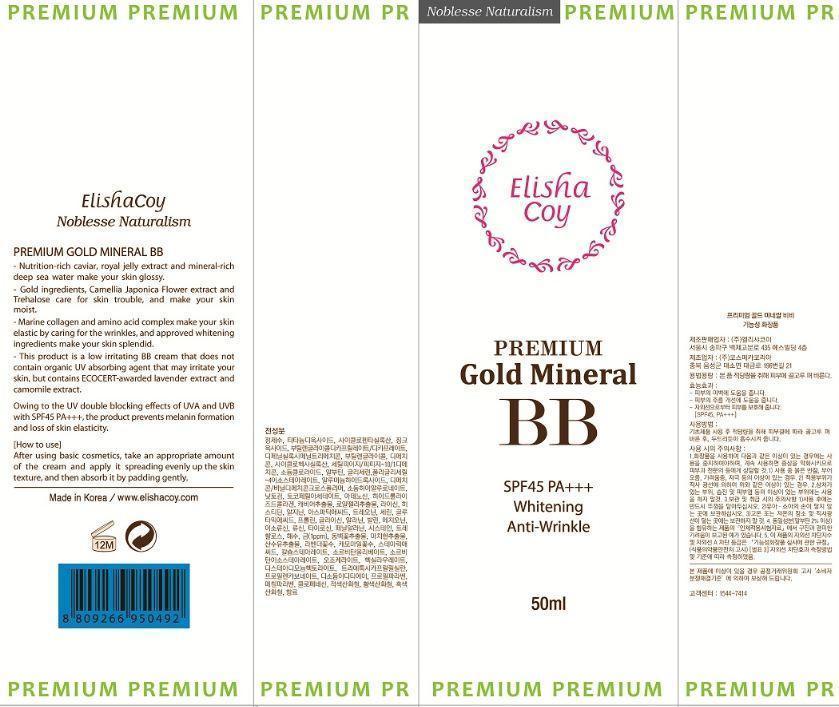 DRUG LABEL: Premium Gold Mineral BB
NDC: 53727-102 | Form: CREAM
Manufacturer: Cosmecca Korea Co., Ltd.
Category: otc | Type: HUMAN OTC DRUG LABEL
Date: 20140815

ACTIVE INGREDIENTS: TITANIUM DIOXIDE 5 g/50 g; ZINC OXIDE 3 g/50 g
INACTIVE INGREDIENTS: WATER; CYCLOMETHICONE 5; BUTYLENE GLYCOL DICAPRYLATE/DICAPRATE; PHENYL TRIMETHICONE; BUTYLENE GLYCOL; DIMETHICONE; CYCLOMETHICONE 6; CETYL PEG/PPG-10/1 DIMETHICONE (HLB 2); SODIUM CHLORIDE; ARBUTIN; POLYGLYCERYL-4 ISOSTEARATE; GLYCERIN; ALUMINUM HYDROXIDE; DIMETHICONE/VINYL DIMETHICONE CROSSPOLYMER (HARD PARTICLE); HYALURONATE SODIUM; .ALPHA.-TOCOPHEROL ACETATE; ADENOSINE; GELATIN; CAVIAR, UNSPECIFIED; ROYAL JELLY; LYSINE; HISTIDINE; ARGININE; ASPARTIC ACID; THREONINE; SERINE; GLUTAMIC ACID; PROLINE; GLYCINE; ALANINE; VALINE; METHIONINE; ISOLEUCINE; LEUCINE; TYROSINE; PHENYLALANINE; CYSTEINE; TREHALOSE; GOLD; CAMELLIA JAPONICA FLOWER; PORTULACA OLERACEA WHOLE; CORNUS OFFICINALIS FRUIT; LAVANDULA ANGUSTIFOLIA WHOLE; MATRICARIA CHAMOMILLA FLOWERING TOP OIL; STEARIC ACID; CALCIUM STEARATE; SORBITAN OLIVATE; SORBITAN ISOSTEARATE; CERESIN; HEXYL LAURATE; DISTEARDIMONIUM HECTORITE; TRIETHOXYCAPRYLYLSILANE; PROPYLENE CARBONATE; EDETATE DISODIUM; PROPYLPARABEN; METHYLPARABEN; CHLORPHENESIN; FERRIC OXIDE RED

ACTIVE INGREDIENT

Titanium Dioxide (9.92%), Zinc Oxide (6.31%)

PURPOSE

Premium Gold Mineral BB

SPF45 PA+++

Whitening

Anti-Wrinkle

Keep out of reach of children

INDICATIONS AND USAGE

Elishacoy

Noblesse Naturalism

Premium Gold Mineral BB

- Nutrition-rich caviar, royal jelly extract and mineral-rich deep sea water make your skin glossy.

- Gold ingredients, Cammelia Japonica Flower extract and Trehalose care for skin trouble, and make your skin moist.

- Marine collagen and amino acid complex make your skin elastic by caring for the wrinkles, and approved whitening ingredients make your skin splendid.

- This product is a low irritating BB cream that does not contain organic UV absorbing agent that may irritate your skin, but contains ECOCERT-awarded lavender extract and camomile extract.

Owing to the UV double blocking effects of UVA and UVB with SPF45 PA+++, the product prevents melanin formation and loss of skin elasticity.

Warnings

DOSAGE AND ADMINISTRATION

[How to Use]

After using basic cosmetics, take an appropriate amount of the cream and apply it spreading evenly up the skin texture, and then absorb it by padding gently.

INACTIVE INGREDIENT

Water, Cyclopentasiloxane, Butylene Glycol Dicaprylate/Dicaprate, Phenyl Trimethicone, Butylene Glycol, Dimethicone, Cyclohexasiloxane, Cetyl PEG/PPG-10/1 Dimethicone, Sodium Chloride, Arbutin, Polyglyceryl-4 Isostearate, Glycerin, Aluminum Hydroxide, Dimethicone/Vinyl Dimethicone, Crosspolymer, Sodium Hyaluronate, Natto Gum, Tocopheryl Acetate, Adenosine, Hydrolyzed Collagen, Caviar Extract, Royal Jelly Extract, Lysine, Histidine, Arginine, Aspartic Acid, Threonine, Serine, Glutamic Acid, Proline, Glycine, Alanine, Valine, Methionine, Isoleucine, Leucine, Tyrosine, Phenylalanine, Cysteine, Trehalose, Sea Water, Gold, Camellia Japonica Flower Extract, Portulaca Oleracea Extract, Cornus Officinalis Fruit Extract, Lavandula Angustifolia (Lavender) Flower/Leaf/Stem Extract, Chamomilla Recutita (Matricaria) Flower Extract, Stearic Acid, Calcium Stearate, Sorbitan Olivate, Sorbitan Isostearate, Ozokerite, Hexyl Laurate, Disteardimonium Hectorite, Triethoxycaprylylsilane, Propylene Carbonate, Disodium EDTA, Propylparaben, Methylparaben, Chlorphenesin, Fragrance, Iron Oxides